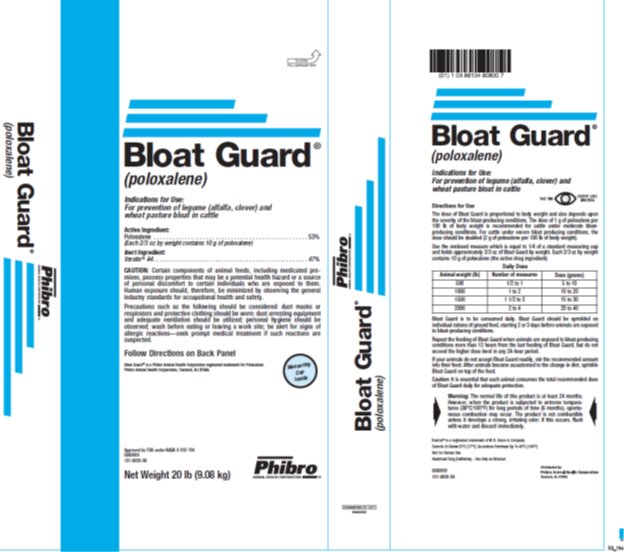 DRUG LABEL: Bloat Guard
NDC: 66104-6080 | Form: POWDER
Manufacturer: Phibro Animal Health
Category: animal | Type: OTC TYPE A MEDICATED ARTICLE ANIMAL DRUG LABEL
Date: 20220127

ACTIVE INGREDIENTS: POLOXALENE 240.4 g/0.45 kg

Bloat Guard Top Dressing for Feed® (poloxalene)

Medicated Top Dressing for Feed

Indications for Use:

For prevention of legume (alfalfa, clover) and wheat pasture bloat in cattle

Active Ingredient

Poloxalene . . . . . . . . . . . . . . . . . . . . . . . . . . . . . . . . . . . . . . . . . . . . . . . . . . . 53%
(Each 2/3 oz by weight of top dressing contains 10 g of poloxalene)

Inert Ingredient:

Verxite® #4. . . . . . . . . . . . . . . . . . . . . . . . . . . . . . . . . . . . . . . . . . . . . . . . . . . 47%

CAUTION:

Certain components of animal feeds, including medicated premixes, possess properties that may be a potential health hazard or a source of personal discomfort to certain individuals who are exposed to them. Human exposure should, therefore, be minimized by observing the general industry standards for occupational health and safety.

Precautions such as the following should be considered: dust masks or respirators and protective clothing should be worn; dust arresting equipment and adequate ventilation should be utilized; personal hygiene should be observed; wash before eating or leaving a work site; be alert for signs of allergic reactions—seek prompt medical treatment if such reactions are suspected.

Follow Directions on Back Panel

Bloat Guard® is a Phibro Animal Health Corporation registered trademark for Poloxalene.

Phibro Animal Health Corporation, Teaneck, NJ 07666.

Approved by FDA under NADA #032-704

6080000

101-9030-09

Directions for Use The dose of Bloat Guard is proportional to body weight and also depends upon the severity of the bloat-producing conditions. The dose of 1 g of poloxalene per 100 lb of body weight is recommended for cattle under moderate bloat-producing conditions. For cattle under severe bloat producing conditions, the dose should be doubled (2 g of poloxalene per 100 lb of body weight). Use the enclosed measure which is equal to 1/4 of a standard measuring cup and holds approximately 2/3 oz of Bloat Guard by weight. Each 2/3 oz by weight contains 10 g of poloxalene (the active drug ingredient). Daily DoseAnimal WeightNumber of measuresDose (grams)500½ to 15 to 1010001 to 210 to 2015001 ½ to 315 to 3020002 to 420 to 40

Bloat Guard is to be consumed daily. Bloat Guard should be sprinkled on individual rations of ground feed, starting 2 or 3 days before animals are exposed to bloat-producing conditions.

Repeat the feeding of Bloat Guard when animals are exposed to bloat-producing conditions more than 12 hours from the last feeding of Bloat Guard, but do not exceed the higher dosage levels in any 24-hour period.

If your animals do not accept Bloat Guard readily, stir the recommended amount into their feed. After animals become accustomed to the change in diet, sprinkle Bloat Guard on top of the feed.

Caution: It is essential that each animal consumes the total recommended dosage of Bloat Guard daily for adequate protection.

Warning:

The normal life of this product is at least 24 months. However, when the product is subjected to extreme temperatures (38°C/100°F) for long periods of time (6 months), spontaneous combustion may occur. The product is not combustible unless it develops a strong, irritating odor; if this occurs, flush with water and discard immediately.

Verxite® is a registered trademark of W.R. Grace & Company.

Store At or Below 25°C (77°F), Excursions Permitted Up To 40°C (104°F)

NOT FOR HUMAN USE

Restricted Drug (California) – Use Only As Directed

Bloat Guard® is a Phibro Animal Health registered trademark for Poloxalene

Distributed by:

Phibro Animal Health Corporation, Teaneck, NJ 07666.

6080000

101-9030-09